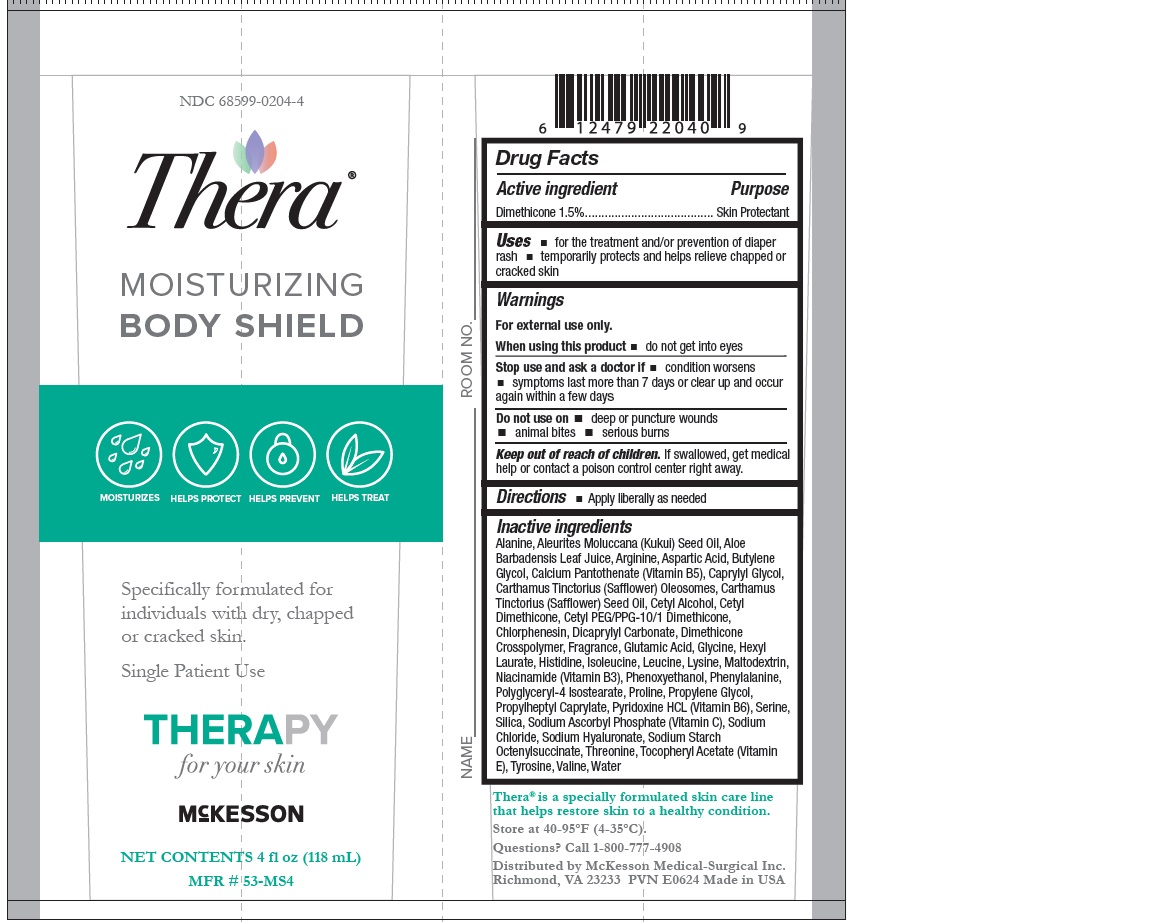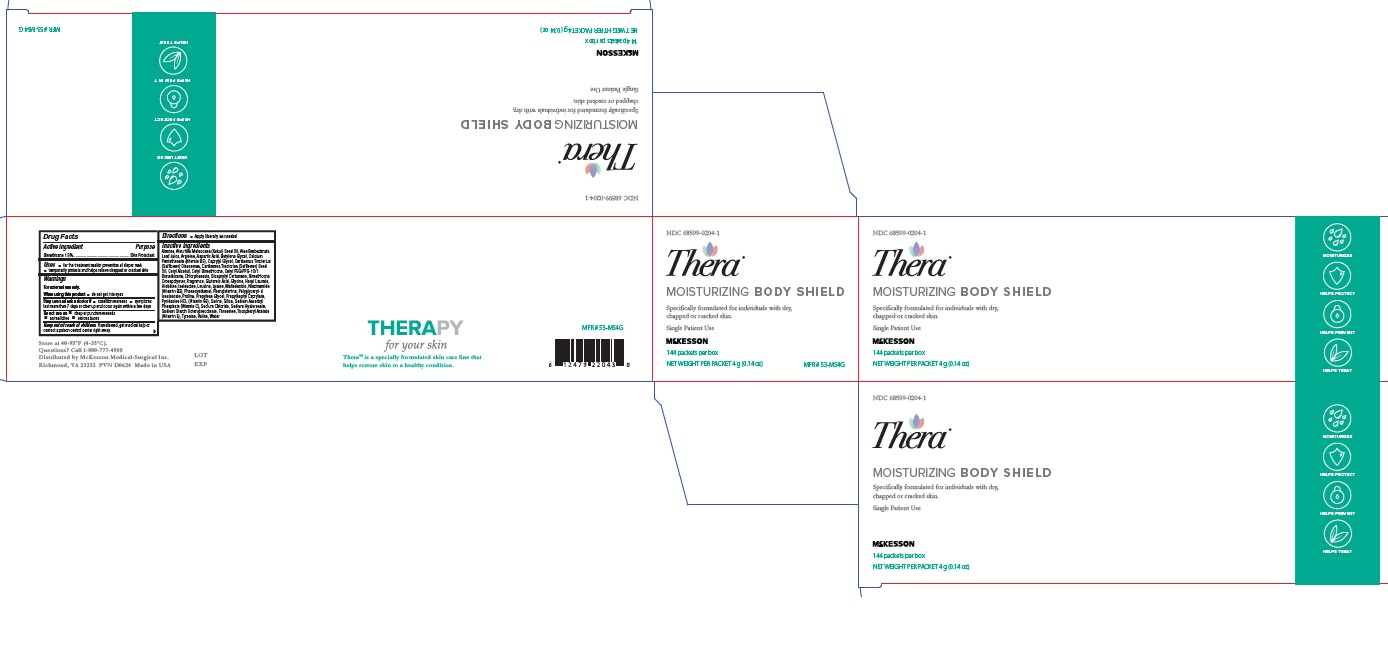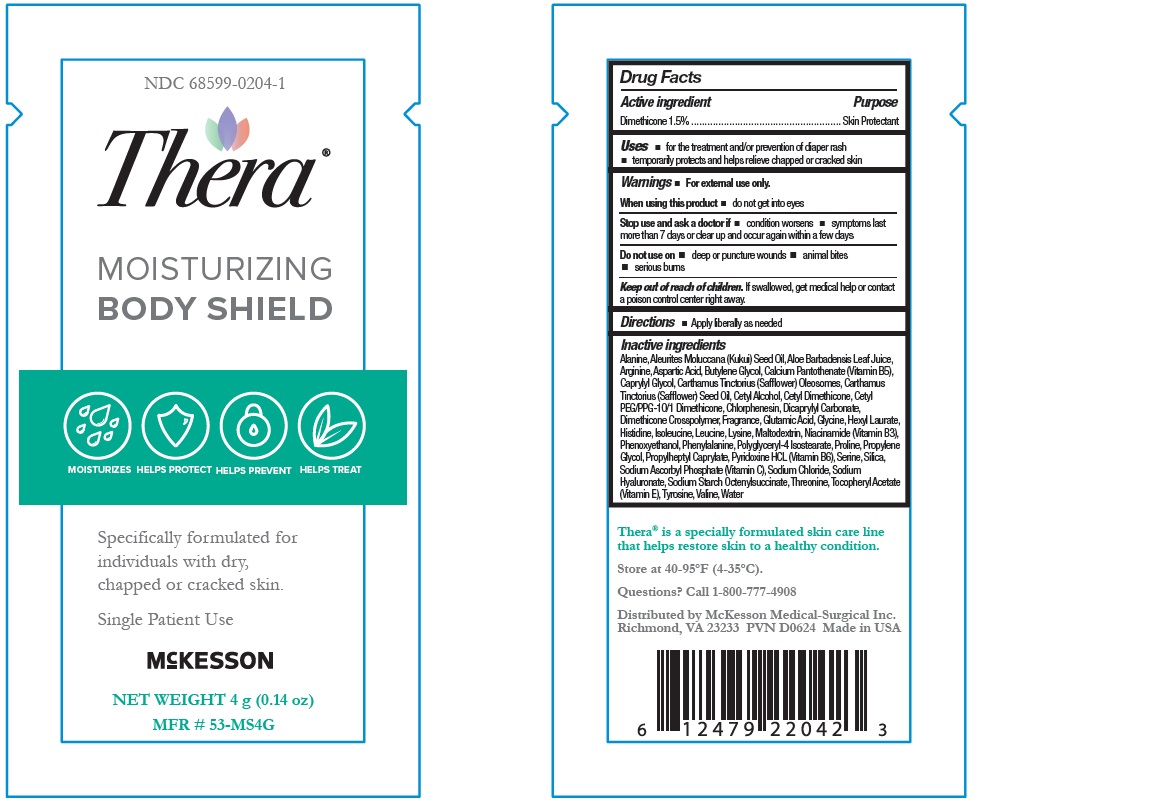 DRUG LABEL: THERA Moisturizing Body Shield
NDC: 68599-0204 | Form: CREAM
Manufacturer: McKesson Medical-Surgical Inc.
Category: otc | Type: HUMAN OTC DRUG LABEL
Date: 20240618

ACTIVE INGREDIENTS: DIMETHICONE 15 mg/1 g
INACTIVE INGREDIENTS: GLUTAMIC ACID; THREONINE; CHLORPHENESIN; LYSINE; POLYGLYCERYL-4 ISOSTEARATE; GLYCINE; SERINE; HEXYL LAURATE; HISTIDINE; ALANINE; SAFFLOWER OIL; CETYL PEG/PPG-10/1 DIMETHICONE (HLB 2); BUTYLENE GLYCOL; SILICON DIOXIDE; HYALURONATE SODIUM; ISOLEUCINE; TYROSINE; VALINE; KUKUI NUT OIL; ALOE VERA LEAF; CALCIUM PANTOTHENATE; MALTODEXTRIN; NIACINAMIDE; PYRIDOXINE HYDROCHLORIDE; SODIUM ASCORBYL PHOSPHATE; .ALPHA.-TOCOPHEROL ACETATE, DL-; ARGININE; CARTHAMUS TINCTORIUS SEED OLEOSOMES; CAPRYLYL GLYCOL; DICAPRYLYL CARBONATE; PHENOXYETHANOL; PROPYLENE GLYCOL; PROPYLHEPTYL CAPRYLATE; WATER; LEUCINE; PHENYLALANINE; SODIUM CHLORIDE; PROLINE; CETYL ALCOHOL; ASPARTIC ACID

Drug Facts

Active ingredient

- Dimethicone 1.5%

Purpose

- Skin Protectant

Keep out of reach of children

- If swallowed, get medical help or contact a Poison Control Center right away.

Uses

- For the treatment and/or prevention of diaper rash
- Temporarily protects and helps relieve chapped or cracked skin

Warnings

- For external use only
- Protect from freezing. Avoid excessive heat.

Do not use on

- deep or puncture wounds
- animal bites
- serious burns

When using this product

- do not get into eyes

Stop use and ask a doctor if

- condition worsens
- symptoms last more than 7 days or clear up and occur again within a few days

Directions

- Apply liberally as needed

Inactive ingredients

Alanine, Aleurites Moluccana (Kukui) Seed Oil, Aloe
Barbadensis Leaf Juice, Arginine, Aspartic Acid, Butylene
Glycol, Calcium Pantothenate (Vitamin B5), Caprylyl Glycol,
Carthamus Tinctorius (Safflower) Oleosomes, Carthamus
Tinctorius (Safflower) Seed Oil, Cetyl Alcohol, Cetyl
Dimethicone, Cetyl PEG/PPG-10/1 Dimethicone,
Chlorphenesin, Dicaprylyl Carbonate, Dimethicone
Crosspolymer, Fragrance, Glutamic Acid, Glycine, Hexyl
Laurate, Histidine, Isoleucine, Leucine, Lysine, Maltodextrin,
Niacinamide (Vitamin B3), Phenoxyethanol, Phenylalanine,
Polyglyceryl-4 Isostearate, Proline, Propylene Glycol,
Propylheptyl Caprylate, Pyridoxine HCL (Vitamin B6), Serine,
Silica, Sodium Ascorbyl Phosphate (Vitamin C), Sodium
Chloride, Sodium Hyaluronate, Sodium Starch
Octenylsuccinate, Threonine, Tocopheryl Acetate (Vitamin
E), Tyrosine, Valine, Water

Label (4 oz)

NDC 68599-0204-4

Thera

Moisturizing Body Shield

Net Contents 4 fl oz (118 mL)

MFR# 53-MS4

Label (4g)

NDC 68599-0204-1

Thera

Moisturizing Body Shield

Net Contents 4 g (0.14 oz)

MFR# 53-MS4G